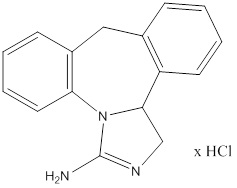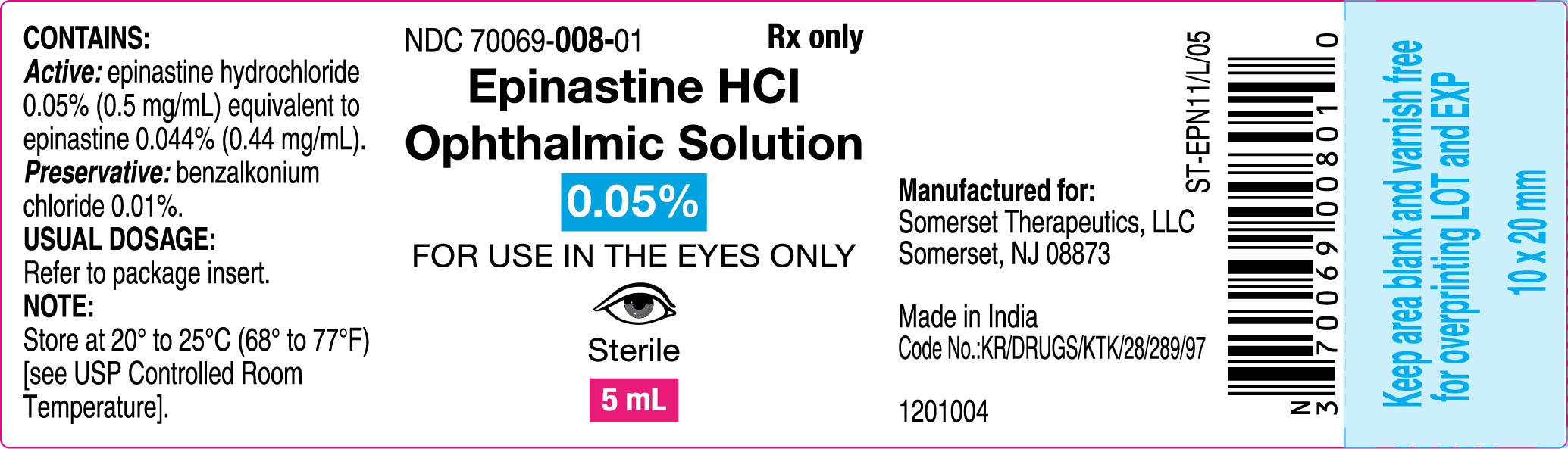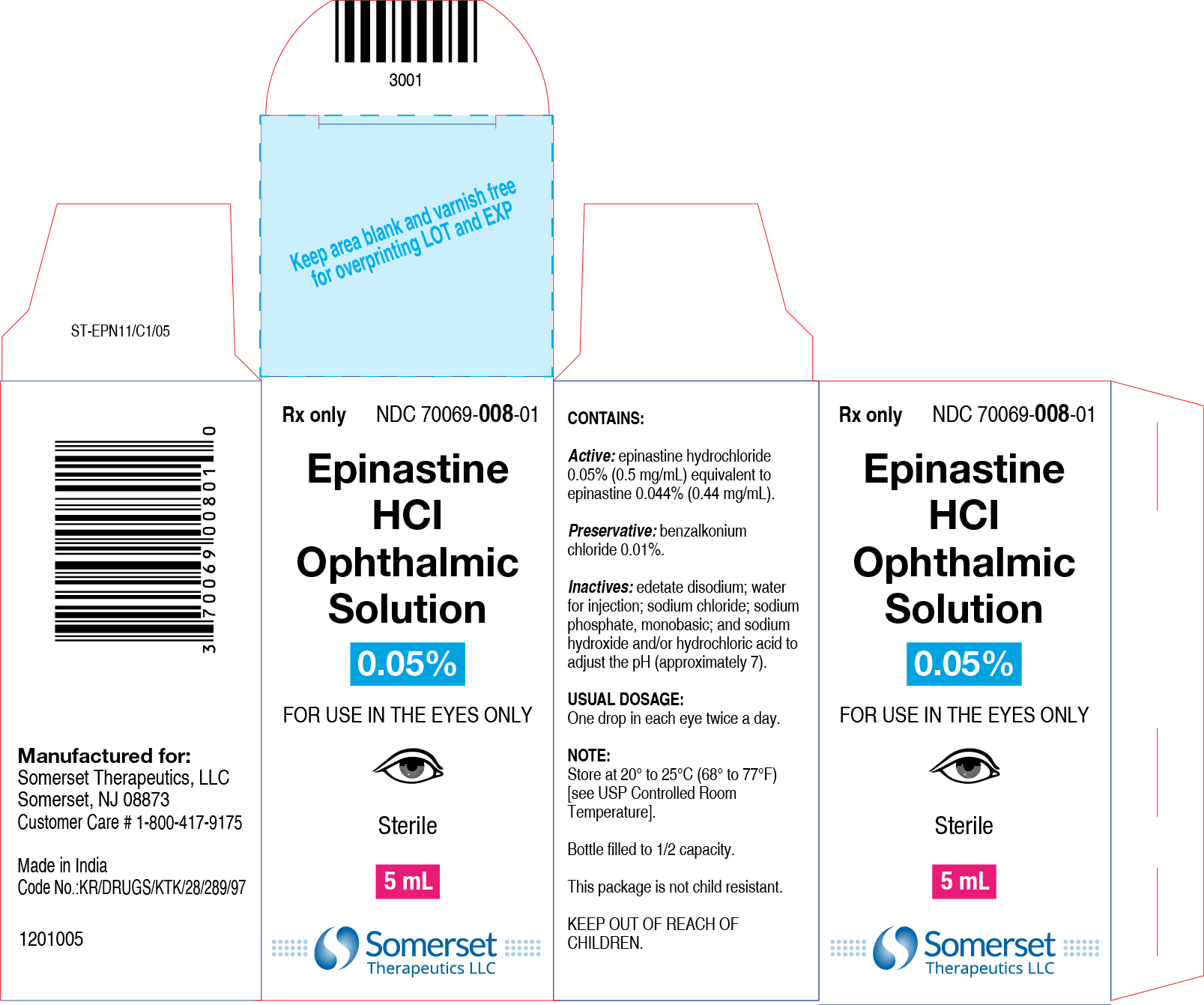 DRUG LABEL: EPINASTINE HYDROCHLORIDE
NDC: 70069-008 | Form: SOLUTION/ DROPS
Manufacturer: Somerset Therapeutics, LLC
Category: prescription | Type: HUMAN PRESCRIPTION DRUG LABEL
Date: 20250322

ACTIVE INGREDIENTS: EPINASTINE HYDROCHLORIDE 0.5 mg/1 mL
INACTIVE INGREDIENTS: BENZALKONIUM CHLORIDE 0.1 mg/1 mL; EDETATE DISODIUM; SODIUM CHLORIDE; SODIUM PHOSPHATE, MONOBASIC; SODIUM HYDROXIDE; HYDROCHLORIC ACID; WATER

HIGHLIGHTS OF PRESCRIBING INFORMATION

These highlights do not include all the information needed to use EPINASTINE HCl safely and effectively. See full prescribing information for EPINASTINE HCl.
EPINASTINE HCl Ophthalmic Solution 0.05%
Initial U.S. Approval: 2003

1 INDICATIONS AND USAGE

Epinastine HCl ophthalmic solution is an H1 histamine receptor antagonist indicated for the prevention of itching associated with allergic conjunctivitis.

2 DOSAGE AND ADMINISTRATION

The recommended dosage is one drop in each eye twice a day.

3 DOSAGE FORMS AND STRENGTHS

Ophthalmic solution containing 0.5 mg/mL epinastine HCl.

4 CONTRAINDICATIONS

None

5 WARNINGS AND PRECAUTIONS

- To minimize the risk of contamination, do not touch dropper tip to any surface. Keep bottle tightly closed when not in use. (5.1)
- Epinastine HCl should not be used to treat contact lens-related irritation. (5.2)
- Remove contact lenses prior to instillation of epinastine HCl.(5.2)

6 ADVERSE REACTIONS

The most common ocular adverse reactions (incidence occurring in approximately 1% to 10% of epinastine HCl-treated eyes were burning sensation in the eye, folliculosis, hyperemia, and pruritus. The most common non-ocular adverse reactions, occurring in 10% epinastine HCl-treated eyes, were infection (cold symptoms and upper respiratory infections).

To report SUSPECTED ADVERSE REACTIONS, contact Somerset Therapeutics, LLC at +1 800-417-9175 or FDA at 1-800-FDA-1088 or www.fda.gov/medwatch.

FULL PRESCRIBING INFORMATION

1 INDICATIONS AND USAGE

Epinastine HCl ophthalmic solution is indicated for the prevention of itching associated with allergic conjunctivitis.

2 DOSAGE AND ADMINISTRATION

The recommended dosage is one drop in each eye twice a day.

Treatment should be continued throughout the period of exposure (i.e., until the pollen season is over or until exposure to the offending allergen is terminated), even when symptoms are absent.

3 DOSAGE FORMS AND STRENGTHS

Solution containing 0.5 mg/mL epinastine HCl.

4 CONTRAINDICATIONS

None

5 WARNINGS AND PRECAUTIONS

5.1 Contamination of Tip and Solution

Patients should be instructed to avoid allowing the tip of the dispensing container to contact the eye, surrounding structures, fingers, or any other surface in order to avoid contamination of the solution by common bacteria known to cause ocular infections. Serious damage to the eye and subsequent loss of vision may result from using contaminated solutions.

Bottle should be kept tightly closed when not in use.

5.2 Use with Contact Lenses

Patients should be advised not to wear a contact lens if their eye is red. Epinastine HCl ophthalmic solution should not be used to treat contact lens-related irritation.

The preservative in epinastine HCl, benzalkonium chloride, may be absorbed by soft contact lenses. Contact lenses should be removed prior to instillation of epinastine HCl ophthalmic solution and may be reinserted after 10 minutes following its administration.

5.3 Topical Ophthalmic Use Only

Epinastine HCl ophthalmic solution is for topical ophthalmic use only and not for injection or oral use.

6 ADVERSE REACTIONS

6.1 Clinical Studies Experience

Because clinical studies are conducted under widely varying conditions, adverse reaction rates observed in the clinical studies of a drug cannot be directly compared to rates in the clinical studies of another drug and may not reflect the rates observed in practice.

The most frequently reported ocular adverse reactions occurring in approximately 1 to 10% of patients were burning sensation in the eye, folliculosis, hyperemia, and pruritus.

The most frequently reported non-ocular adverse reactions were infection (cold symptoms and upper respiratory infections), seen in approximately 10% of patients, and headache, rhinitis, sinusitis, increased cough, and pharyngitis, seen in approximately 1 to 3% of patients.

Some of these reactions were similar to the underlying disease being studied.

6.2 Postmarketing Experience

The following reactions have been identified during postmarketing use of epinastine HCl in clinical practice. Because they are reported voluntarily from a population of unknown size, estimates of frequency cannot be made. The reactions, which have been chosen for inclusion due to either their seriousness, frequency of reporting, possible causal connection to epinastine HCl, or a combination of these factors, include: lacrimation increased.

8 USE IN SPECIFIC POPULATIONS

8.1 Pregnancy:

In an embryofetal developmental study in pregnant rats, maternal toxicity with no embryofetal effects was observed at an oral dose that was approximately 150,000 times the maximum recommended ocular human dose (MROHD) of 0.0014 mg/kg/day on a mg/kg basis. Total resorptions and abortion were observed in an embryofetal study in pregnant rabbits at an oral dose that was approximately 55,000 times the MROHD. In both studies, no drug-induced teratogenic effects were noted.

Epinastine reduced pup body weight gain following an oral dose to pregnant rats that was approximately 90,000 times the MROHD.

There are, however, no adequate and well-controlled studies in pregnant women. Because animal reproduction studies are not always predictive of human response, epinastine HCl ophthalmic solution should be used during pregnancy only if the potential benefit justifies the potential risk to the fetus.

8.3 Nursing Mothers

A study in lactating rats revealed excretion of epinastine in the breast milk. It is not known whether this drug is excreted in human milk. Because many drugs are excreted in human milk, caution should be exercised when epinastine HCl ophthalmic solution is administered to a nursing woman.

8.4 Pediatric Use

Safety and effectiveness in pediatric patients below the age of 2 years have not been established.

8.5 Geriatric Use

No overall differences in safety or effectiveness have been observed between elderly and younger patients.

11 DESCRIPTION

Epinastine HCl Ophthalmic Solution 0.05% is a clear, colorless, sterile isotonic solution containing epinastine HCl, an antihistamine and an inhibitor of histamine release from the mast cell for topical administration to the eyes.

Epinastine HCl is represented by the following structural formula:

C16H15N3HCl Mol. Wt. 285.78

Chemical Name: 3-Amino-9,13b-dihydro-1H-dibenz[c,f]imidazo [1,5-a]azepine hydrochloride

Each mL contains: Active: epinastine HCl 0.05% (0.5 mg/mL) equivalent to epinastine 0.044% (0.44 mg/mL); Preservative: benzalkonium chloride 0.01%; Inactives: edetate disodium; water for injection; sodium chloride; sodium phosphate, monobasic; and sodium hydroxide and/or hydrochloric acid (to adjust pH). Epinastine HCl has a pH of approximately 7 and an osmolality range of 250 to 310 mOsm/kg.

12 CLINICAL PHARMACOLOGY

12.1 Mechanism of Action

Epinastine is a topically active, direct H1-receptor antagonist and an inhibitor of the release of histamine from the mast cell. Epinastine is selective for the histamine H1-receptor and has affinity for the histamine H2-receptor. Epinastine also possesses affinity for the ɑ1, ɑ2-, and 5-HT2-receptors.

12.3 Pharmacokinetics

Fourteen subjects, with allergic conjunctivitis, received one drop of epinastine HCl ophthalmic solution in each eye twice daily for seven days. On day seven, average maximum epinastine plasma concentrations of 0.04±0.014 ng/mL were reached after about two hours indicating low systemic exposure. While these concentrations represented an increase over those seen following a single dose, the day 1 and day 7 Area Under the Curve (AUC) values were unchanged indicating that there is no increase in systemic absorption with multiple dosing. Epinastine is 64% bound to plasma proteins. The total systemic clearance is approximately 56 L/hr and the terminal plasma elimination half-life is about 12 hours. Epinastine is mainly excreted unchanged. About 55% of an intravenous dose is recovered unchanged in the urine with about 30% in feces. Less than 10% is metabolized. The renal elimination is mainly via active tubular secretion.

13 NONCLINICAL TOXICOLOGY

13.1 Carcinogenesis, Mutagenesis, Impairment of Fertility

In 18-month or 2-year dietary carcinogenicity studies in mice or rats, respectively, epinastine was not carcinogenic at doses up to 40 mg/kg [approximately 30,000 times higher than the MROHD, assuming 100% absorption in humans and animals].

Epinastine in newly synthesized batches was negative for mutagenicity in the Ames / Salmonella assay and in vitro chromosome aberration assay using human lymphocytes. Positive results were seen with early batches of epinastine in two in vitro chromosomal aberration studies conducted in the 1980s with human peripheral lymphocytes and with V79 cells, respectively. Epinastine was negative in the in vivo clastogenicity studies, including the mouse micronucleus assay and chromosome aberration assay in Chinese hamsters. Epinastine was also negative in the cell transformation assay using Syrian hamster embryo cells, V79/HGPRT mammalian cell point mutation assay, and in vivo/in vitro unscheduled DNA synthesis assay using rat primary hepatocytes.

Epinastine had no effect on fertility of male rats. Decreased fertility in female rats was observed at an oral dose up to approximately 90,000 times the MROHD.

14 CLINICAL STUDIES

Epinastine HCl 0.05% has been shown to be significantly superior to vehicle for improving ocular itching in patients with allergic conjunctivitis in clinical studies using two different models: (1) conjunctival antigen challenge (CAC) where patients were dosed and then received antigen instilled into the inferior conjunctival fornix; and (2) environmental field studies where patients were dosed and evaluated during allergy season in their natural habitat. Results demonstrated a rapid onset of action for epinastine HCl 0.05% within 3 to 5 minutes after conjunctival antigen challenge. Duration of effect was shown to be 8 hours, making a twice daily regimen suitable. This dosing regimen was shown to be safe and effective for up to 8 weeks, without evidence of tachyphylaxis.

16 HOW SUPPLIED/STORAGE AND HANDLING

Epinastine HCl ophthalmic solution 0.05% is supplied sterile in opaque white LDPE plastic bottles with dropper tips and white polypropylene caps as follows:

5 mL in 10 mL bottle; individually packaged NDC 70069-008-01

Storage: Store at 20° to 25°C (68° to 77°F); excursions permitted to 15° to 30°C (59° to 86°F) (See USP Controlled Room Temperature). Keep bottle tightly closed and out of the reach of children.

17 PATIENT COUNSELING INFORMATION

17.1 Sterility of Dropper Tip

Patients should be advised not to touch dropper tip to any surface, as this may contaminate the contents [see WARNINGS AND PRECAUTIONS, (5.1)]

17.2 Concomitant Use of Contact Lenses

Patients should be advised not to wear a contact lens if their eye is red. Patients should be advised that epinastine HCl should not be used to treat contact lens-related irritation. Patients should also be advised to remove contact lenses prior to instillation of epinastine HCl. The preservative in epinastine HCl ophthalmic solution, benzalkonium chloride, may be absorbed by soft contact lenses. Lenses may be reinserted after 10 minutes following administration of epinastine HCl.

17.3 Topical Ophthalmic Use Only

For topical ophthalmic administration only.

Manufactured for:

Somerset Therapeutics, LLC

Somerset, NJ 08873

Customer Care # 1-800-417-9175

Made in India

Code No.:KR/DRUGS/KTK/28/289/97

ST-EPN11/P/06

1201003

PACKAGE LABEL.PRINCIPAL DISPLAY PANEL

Container label

Carton label